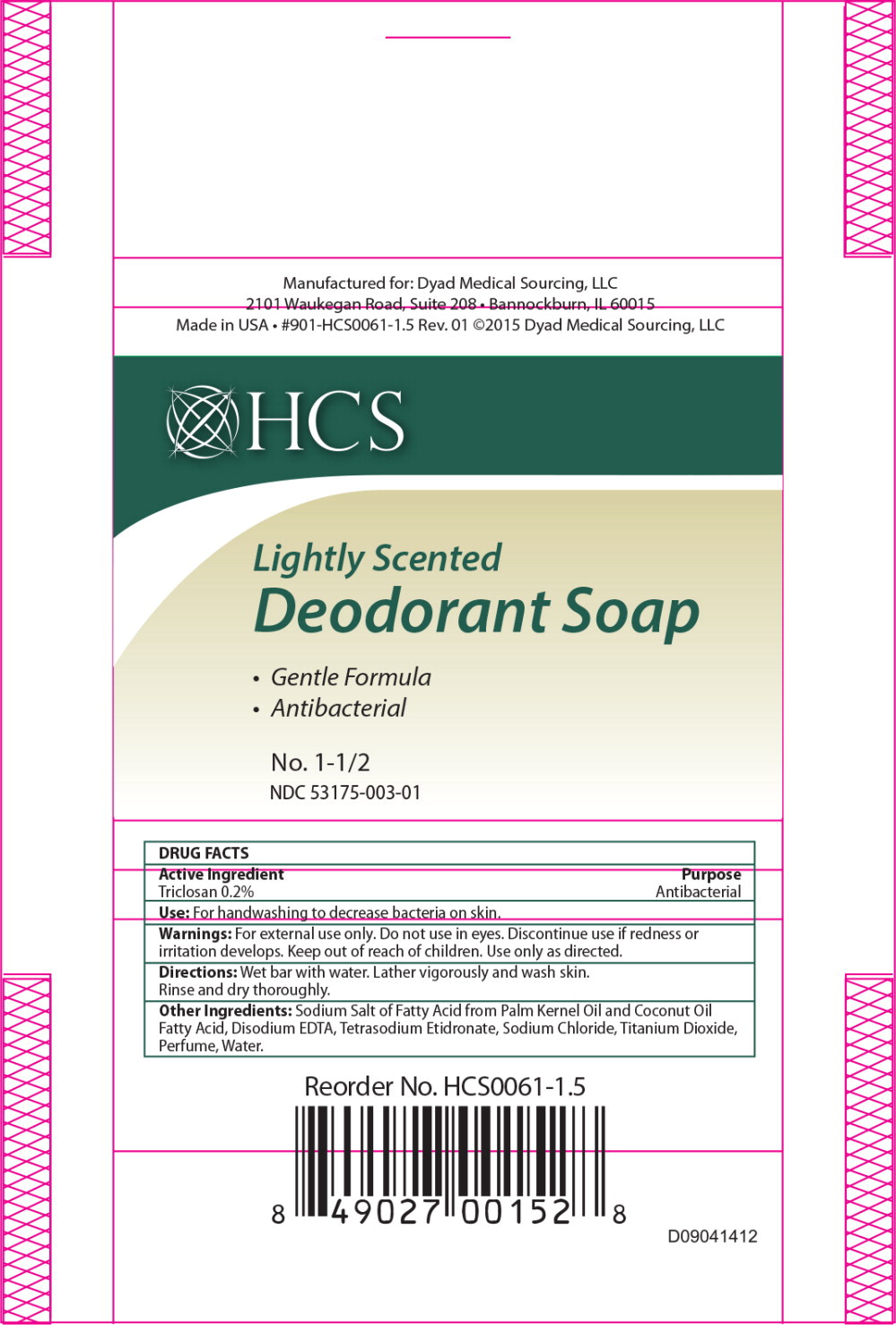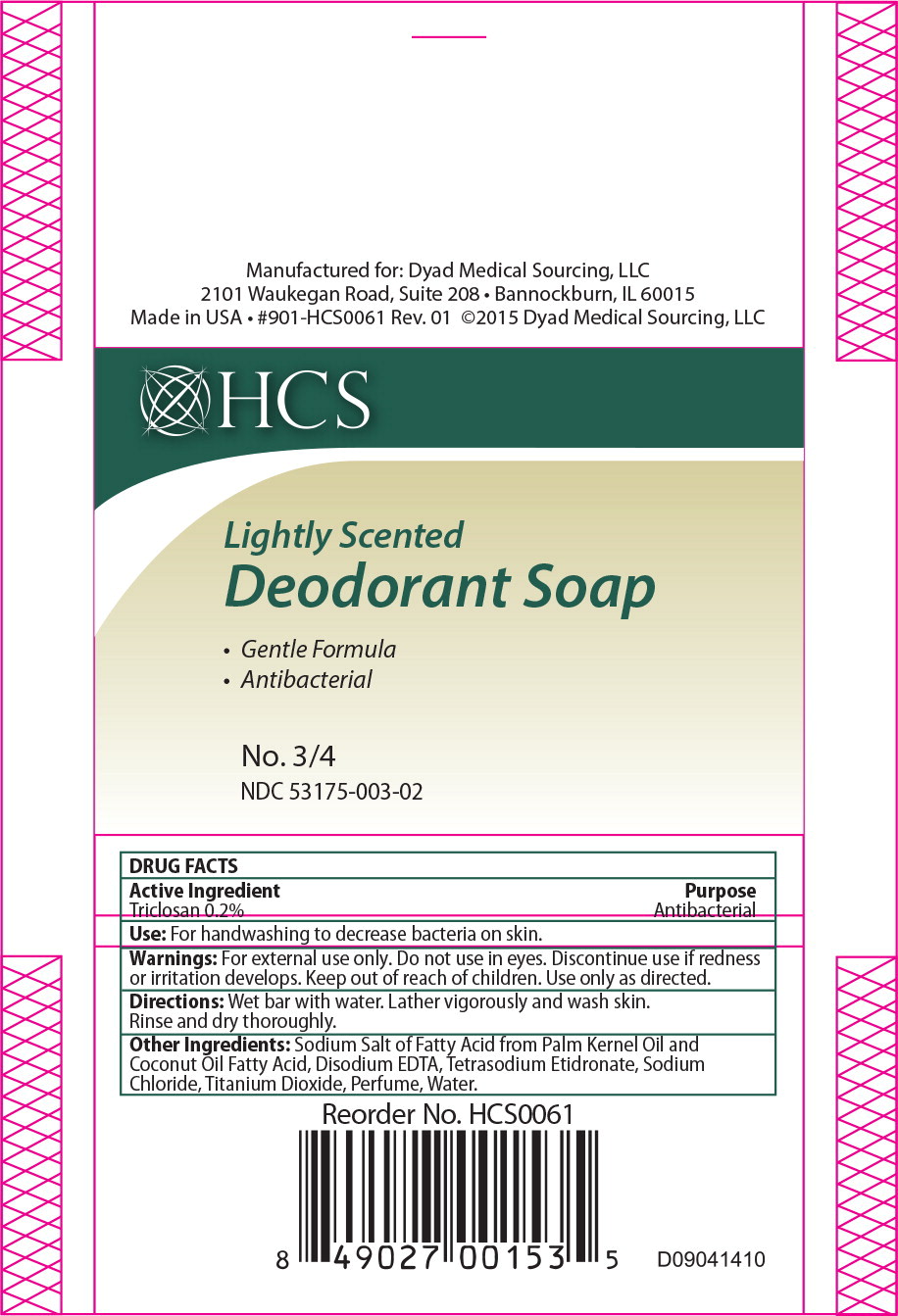 DRUG LABEL: Triclosan
NDC: 53175-003 | Form: SOAP
Manufacturer: Dyad Medical Sourcing, LLC
Category: otc | Type: HUMAN OTC DRUG LABEL
Date: 20150713

ACTIVE INGREDIENTS: Triclosan 0.2 g/100 g
INACTIVE INGREDIENTS: Sodium Cocoate; Sodium Palmate; Water; Glycerin; Sodium Chloride; Titanium Dioxide

Active Ingredient:

Triclosan 0.2%

Purpose:

Antibacterial

Use:

For hand washing to decrease bacteria on skin

Inactive Ingredients:

Sodium Cocoate, Palm Kernelate, Water, Glycerin, Sodium Chloride, Fragrance, Titanium Dioxide.

Warning:

DOSAGE AND ADMINISTRATION

For external use only. Do not use in eyes. Discontinue if redness or irritation develops.

Keep out of reach of children

- Use only as directed

Principal Display Panel - Case Label

HCS

Lightly Scented
Deodorant Soap

- Gentle Formula
- Antibacterial

No. 1-1/2

NDC 53175-003-01

Principal Display Panel - Case Label

HCS

Lightly Scented
Deodorant Soap

- Gentle Formula
- Antibacterial

No. 3/4

NDC 53175-003-02